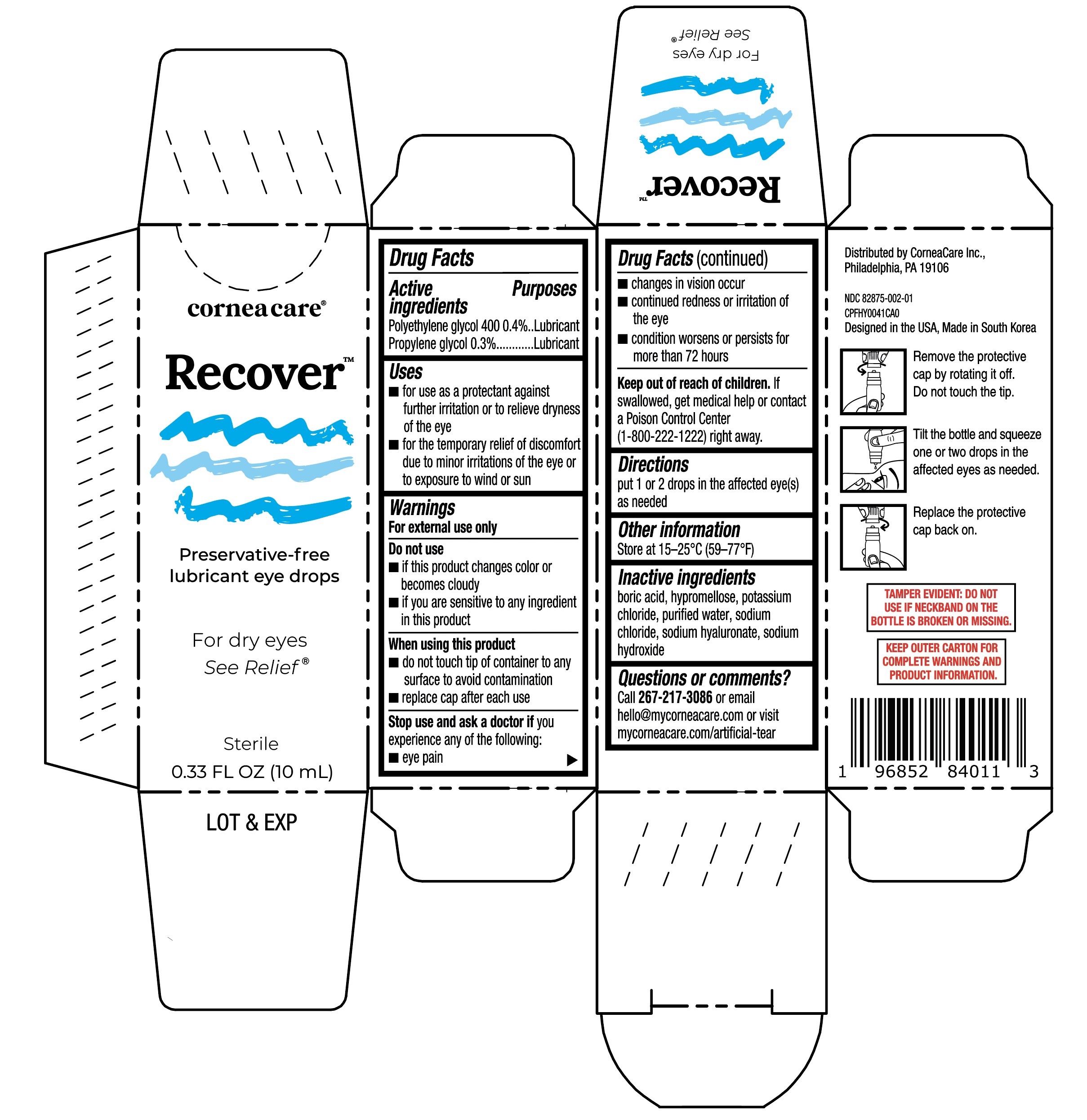 DRUG LABEL: CorneaCare Recover Lubricant Eye Drops
NDC: 82875-002 | Form: SOLUTION/ DROPS
Manufacturer: CorneaCare Inc.
Category: otc | Type: HUMAN OTC DRUG LABEL
Date: 20251230

ACTIVE INGREDIENTS: POLYETHYLENE GLYCOL 400 0.4 g/100 mL; PROPYLENE GLYCOL 0.3 g/100 mL
INACTIVE INGREDIENTS: SODIUM CHLORIDE; HYALURONATE SODIUM; WATER; BORIC ACID; HYPROMELLOSE, UNSPECIFIED; SODIUM HYDROXIDE; POTASSIUM CHLORIDE

CorneaCare Recover Lubricant Eye Drops 10mL (PLD)

Active ingredients

Polyethylene glycol 400 0.4%

Propylene glycol 0.3%

Purposes

Lubricant

Lubricant

Uses

- for use as a protectant against further irritation or to relieve dryness of the eye
- for the temporary relief of discomfort due to minor irritations of the eye or to exposure to wind or sun

Warnings

For external use only

Do not use

- if this product changes color or becomes cloudy
- if you are sensitive to any ingredient in this product

When using this product

- do not touch tip of container to any surface to avoid contamination
- replace cap after each use

Stop use and ask a doctor if

you experience any of the following:

- eye pain
- changes in vision occur
- continued redness or irritation of the eye
- condition worsens or persists for more than 72 hours

Keep out of reach of children.

If swallowed, get medical help or contact a Poison Control Center (1-800-222-1222) right away.

Directions

put 1 or 2 drops in the affected eye(s) as needed

Other information

Store at 15-25°C (59-77°F)

Inactive ingredients

boric acid, hypromellose, potassium chloride, purified water, sodium chloride, sodium hyaluronate, sodium hydroxide

Questions or comments?

Call 267-217-3086 or email hello@mycorneacare.com or visit mycorneacare.com/artificial-tear